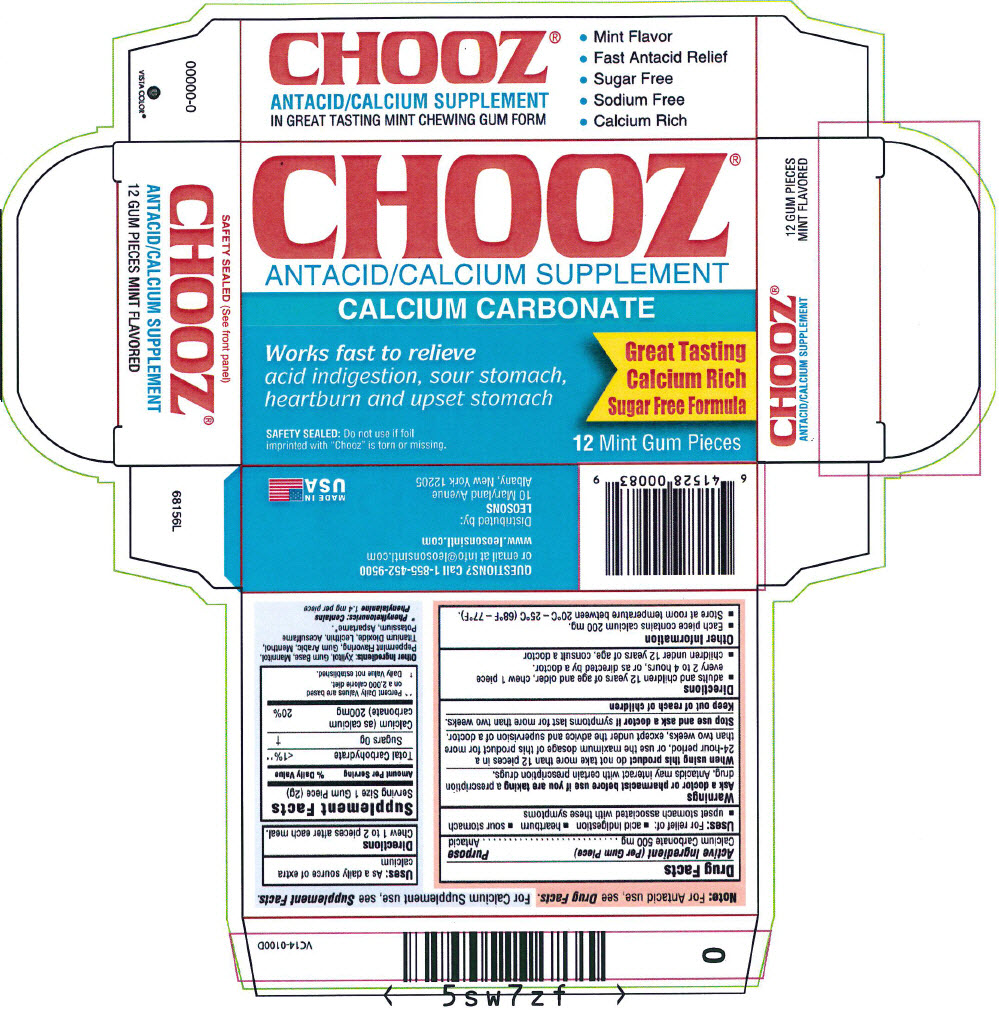 DRUG LABEL: CHOOZ
NDC: 69626-0008 | Form: GUM, CHEWING
Manufacturer: Leosons Overseas Corp.
Category: otc | Type: HUMAN OTC DRUG LABEL
Date: 20241118

ACTIVE INGREDIENTS: CALCIUM CARBONATE 500 mg/1 1
INACTIVE INGREDIENTS: XYLITOL; MANNITOL; ACACIA; MENTHOL, UNSPECIFIED FORM; TITANIUM DIOXIDE; LECITHIN, SOYBEAN; ACESULFAME POTASSIUM; ASPARTAME

CHOOZ®

Drug Facts

Active Ingredient (Per Gum Piece)

Calcium Carbonate 500 mg

Purpose

Active Ingredient (Per Gum Piece) | Purpose
Calcium Carbonate 500 mg................................................................ | Antacid

Uses

For relief of:

- acid indigestion
- heartburn
- sour stomach
- upset stomach associated with these symptoms

Warnings

Ask a doctor or pharmacist before use if you are taking

a prescription drug. Antacids may interact with certain prescription drugs.

When using this product

do not take more than 12 pieces in a 24-hour period, or use the maximum dosage of this product for more than two weeks, except under the advice and supervision of a doctor.

Stop use and ask a doctor if

symptoms last for more than two weeks.

Keep out of reach of children

Directions

- adults and children 12 years of age and older, chew 1 piece every 2 to 4 hours, or as directed by a doctor.
- children under 12 years of age, consult a doctor

Other Information

- Each piece contains calcium 200 mg.
- Store at room temperature between 20°C – 25°C (68°F – 77°F).

Uses:

As a daily source of extra calcium

Directions

Chew 1 to 2 pieces after each meal.

Supplement Facts

Serving Size 1 Gum Piece (2g)
Amount Per Serving | % Daily Value
Total Carbohydrate |  | <1% [Percent Daily Values are based on a 2,000 calorie diet.]
Sugars 0g |  | [Daily Value not established.]
Calcium (as calcium carbonate) 200mg |  | 20%

Other Ingredients

Xylitol, Gum Base, Mannitol, Peppermint Flavoring, Gum Arabic, Menthol, Titanium Dioxide, Lecithin, Acesulfame Potassium, Aspartame [Phenylketonurics: Contains Phenylalanine 1.4 mg per piece] .

QUESTIONS?

Call 1-855-452-9500 or email at info@leosonsintl.com

Distributed by:
LEOSONS
10 Maryland Avenue
Albany, New York 12205

PRINCIPAL DISPLAY PANEL - 12 Gum Piece Blister Pack Box

CHOOZ®
ANTACID/CALCIUM SUPPLEMENT

CALCIUM CARBONATE

Works fast to relieve
acid indigestion, sour stomach,
heartburn and upset stomach

Great Tasting
Calcium Rich
Sugar Free Formula

SAFETY SEALED: Do not use if foil
imprinted with "Chooz" is torn or missing.

12 Mint Gum Pieces